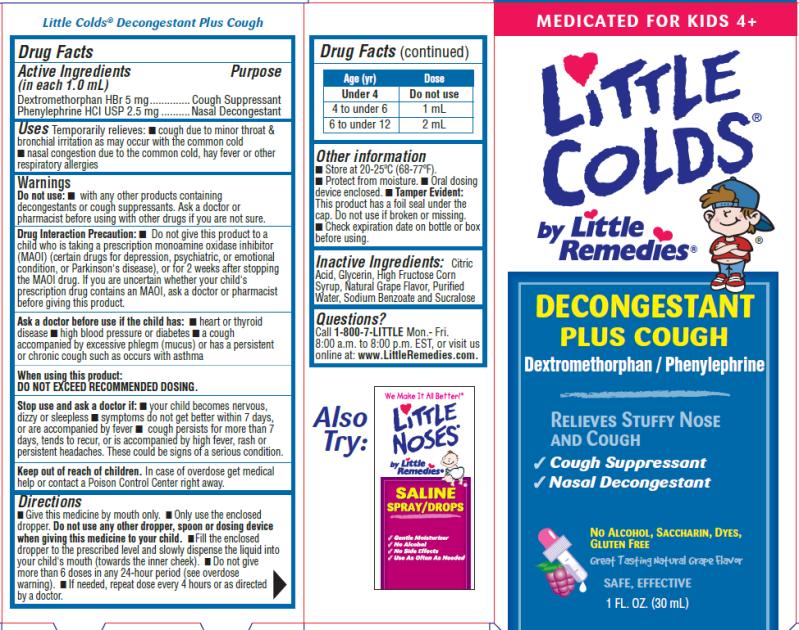 DRUG LABEL: Little Colds Decongestant Plus Cough
NDC: 63029-402 | Form: LIQUID
Manufacturer: Medtech Products Inc.
Category: otc | Type: HUMAN OTC DRUG LABEL
Date: 20101022

ACTIVE INGREDIENTS: DEXTROMETHORPHAN HYDROBROMIDE 5 mg/1.0 mL; PHENYLEPHRINE HYDROCHLORIDE 2.5 mg/1.0 mL
INACTIVE INGREDIENTS: CITRIC ACID; GLYCERIN; HIGH FRUCTOSE CORN SYRUP; WATER; SODIUM BENZOATE; SUCRALOSE

Little Colds Decongestant Plus Cough

Drug Facts

Active Ingredients

(in each 1.0 mL)

Dextromethorphan HBr 5mg

Purpose

Cough Suppressant

Active Ingredients

(in each 1.0 mL)

Phenylephrine HCI USP 2.5mg

Purpose

Nasal Decongestant

Uses

Temporarily relieves:

- cough due to minor throat & bronchial irritation as may occur with the common cold
- nasal congestion due to the common cold, hay fever or other respiratory allergies

Warnings

Do not use:

- with any other products containing decongestants or cough suppressants. Ask a doctor or pharmacist before using with other drugs if you are not sure.
- Do not give this product to a child who is taking a prescription monoamine oxidase inhibitor (MAOI) (certain drugs for depression, psychiatric, or emotional condition, or Parkinson’s disease), or for 2 weeks after stopping the MAOI drug. If you are uncertain whether your child’s prescription drug contains an MAOI, ask a doctor or pharmacist before giving this product.

Drug Interaction Precaution:

Ask a doctor before use if the child has:

- heart or thyroid disease
- high blood pressure or diabetes
- a cough accompanied by excessive phlegm (mucus) or has a persistent or chronic cough such as occurs with asthma

When using this product:

DO NOT EXCEED RECOMMENDED DOSING.

Stop use and ask a doctor if:

- your child becomes nervous, dizzy or sleepless
- symptoms do not get better within 7 days, or are accompanied by fever
- cough persists for more than 7 days, tends to recur, or is accompanied by high fever, rash, or persistent headaches. These could be signs of a serious condition.

Keep out of reach of children.

In case of overdose get medical help or contact a Poison Control Center right away.

Directions

- Give this medicine by mouth only.
- Only use the enclosed dropper. Do not use any other dropper, spoon or dosing device when giving this medicine to your child.
- Fill the enclosed dropper to the prescribed level and slowly dispense the liquid into your child’s mouth (towards the inner cheek).
- Do not give more than 6 doses in any 24-hour period (see overdose warning).
- If needed, repeat dose every 4 hours or as directed by a doctor.

Age (yr) | Dose
Under 4 | Do not use
4 to under 6 | 1 mL
6 to under 12 | 2 mL

Other Information

- Store at 20-25°C (68-77°F)
- Protect from moisture.
- Oral dosing device enclosed.
- Tamper Evident: This product has a foil seal under the cap. Do not use if broken or missing.
- Check expiration date on bottle or box before using.

Inactive Ingredients:

Citric Acid, Glycerin, High Fructose Corn Syrup, Natural Grape Flavor, Purified Water, Sodium Benzoate and Sucralose

Questions?

Call 1-800-7-LITTLE Mon. – Fri. 8:00 a.m. to 8:00 p.m. EST, or visit us online at www.LittleRemedies.com.

PRINCIPAL DISPLAY PANEL

Little Colds® by Little Remedies®
DECONGESTANT PLUS COUGH
Dextromethorphan/Phenylephrine
RELIEVES STUFF NOSE AND COUGH
1 FL. OZ. (30 mL)